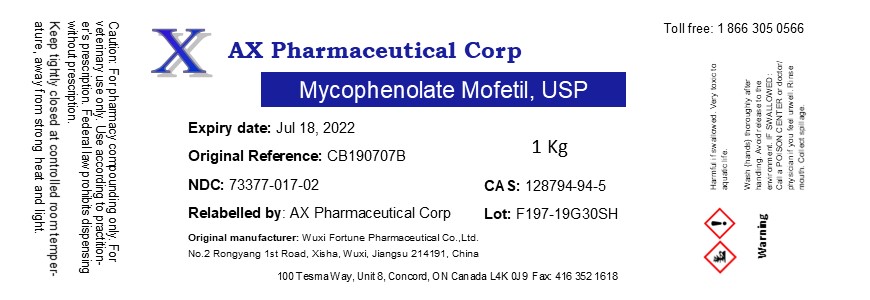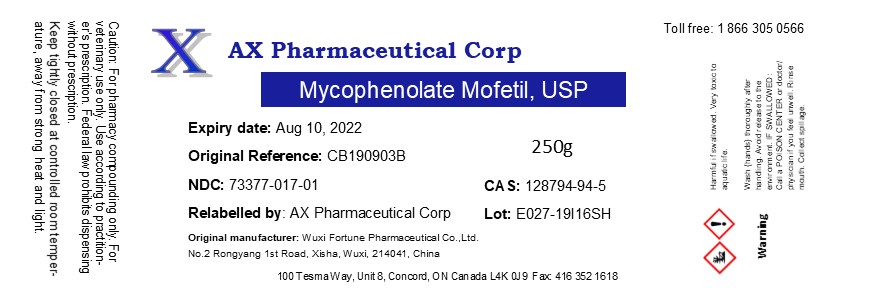 DRUG LABEL: Mycophenolate Mofetil
NDC: 73377-017 | Form: POWDER
Manufacturer: AX Pharmaceutical Corp
Category: other | Type: BULK INGREDIENT
Date: 20210813

ACTIVE INGREDIENTS: MYCOPHENOLATE MOFETIL 1 g/1 g

Mycophenolate Mofetil